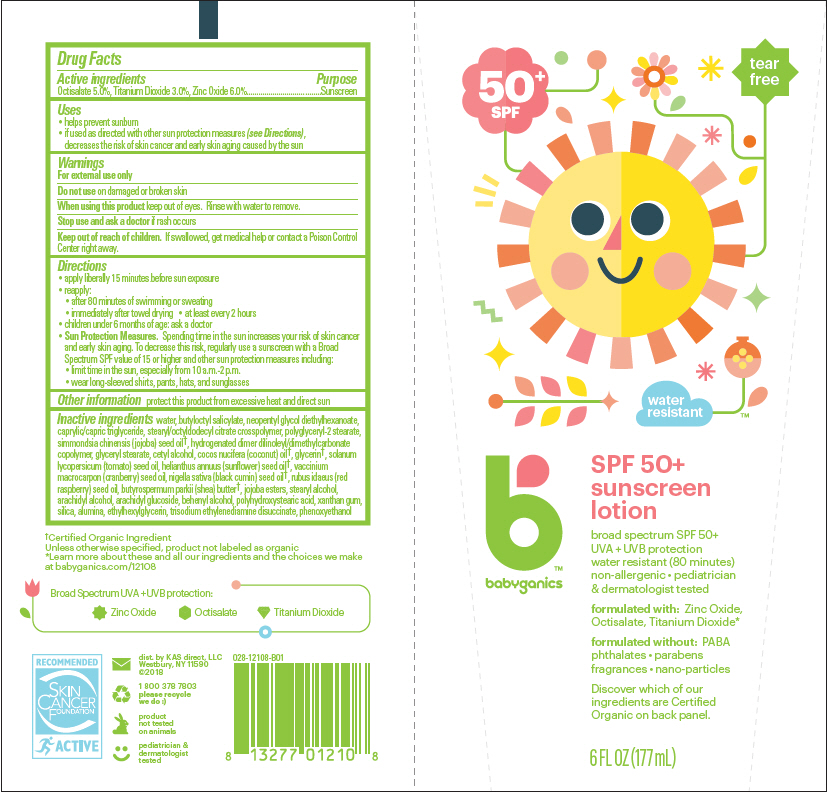 DRUG LABEL: SPF 50 plus Sunscreen
NDC: 59062-1000 | Form: LOTION
Manufacturer: KAS Direct LLC dba BabyGanics
Category: otc | Type: HUMAN OTC DRUG LABEL
Date: 20241217

ACTIVE INGREDIENTS: Titanium Dioxide 30 mg/1 mL; OCTISALATE 50 mg/1 mL; ZINC OXIDE 60 mg/1 mL
INACTIVE INGREDIENTS: WATER; Butyloctyl Salicylate; Neopentyl Glycol Diethylhexanoate; Medium-Chain Triglycerides; Stearyl/Octyldodecyl Citrate Crosspolymer; Polyglyceryl-2 Stearate; CETYL ALCOHOL; Jojoba Oil; Glyceryl Monostearate; GLYCERIN; Coconut Oil; Tomato Seed Oil; Sunflower Oil; ETHYLHEXYLGLYCERIN; Cranberry Seed Oil; Nigella Sativa Seed Oil; Raspberry Seed Oil; PHENOXYETHANOL; XANTHAN GUM; Shea Butter; JOJOBA OIL, RANDOMIZED; Stearyl Alcohol; Arachidyl Alcohol; Arachidyl Glucoside; Docosanol; POLYHYDROXYSTEARIC ACID STEARATE; Silicon Dioxide; Aluminum Oxide; Trisodium Ethylenediamine Disuccinate

SPF 50+ Sunscreen Lotion

Drug Facts

Active ingredients

Octisalate 5.0%, Titanium Dioxide 3.0%, Zinc Oxide 6.0%

Purpose

Sunscreen

Uses

- helps prevent sunburn
- if used as directed with other sun protection measures (see Directions), decreases the risk of skin cancer and early skin aging caused by the sun

Warnings

For external use only

Do not use on damaged or broken skin

When using this product keep out of eyes. Rinse with water to remove.

Stop use and ask a doctor if rash occurs

Keep out of reach of children. If swallowed, get medical help or contact a Poison Control Center right away.

Directions

- apply liberally 15 minutes before sun exposure
- reapply:
  - after 80 minutes of swimming or sweating
  - immediately after towel drying
  - at least every 2 hours
- children under 6 months of age: ask a doctor
- Sun Protection Measures. Spending time in the sun increases your risk of skin cancer and early skin aging. To decrease this risk, regularly use a sunscreen with a Broad Spectrum SPF value of 15 or higher and other sun protection measures including:
  - limit time in the sun, especially from 10 a.m.-2 p.m.
  - wear long-sleeved shirts, pants, hats, and sunglasses

Other information

protect this product from excessive heat and direct sun

Inactive ingredients

water, butyloctyl salicylate, neopentyl glycol diethylhexanoate, caprylic/capric triglyceride, stearyl/octyldodecyl citrate crosspolymer, polyglyceryl-2 stearate, simmondsia chinensis (jojoba) seed oil [Certified Organic Ingredient Unless otherwise specified, product not labeled as organic] , hydrogenated dimer dilinoleyl/dimethylcarbonate copolymer, glyceryl stearate, cetyl alcohol, cocos nucifera (coconut) oil, glycerin, solanum lycopersicum (tomato) seed oil, helianthus annuus (sunflower) seed oil, vaccinium macrocarpon (cranberry) seed oil, nigella sativa (black cumin) seed oil, rubus idaeus (red raspberry) seed oil, butyrospermum parkii (shea) butter, jojoba esters, stearyl alcohol, arachidyl alcohol, arachidyl glucoside, behenyl alcohol, polyhydroxystearic acid, xanthan gum, silica, alumina, ethylhexylglycerin, trisodium ethylenediamine disuccinate, phenoxyethanol

dist. by KAS direct, LLC
Westbury, NY 11590

PRINCIPAL DISPLAY PANEL - 177 mL Tube Label

50^+
SPF

tear
free

water
resistant

babyganics

SPF 50+
sunscreen
lotion

broad spectrum SPF 50+
UVA + UVB protection
water resistant (80 minutes)
non-allergenic • pediatrician
& dermatologist tested

formulated with: Zinc Oxide,
Octisalate, Titanium Dioxide*

formulated without: PABA
phthalates • parabens
fragrances • nano-particles

Discover which of our
ingredients are Certified
Organic on back panel.

6 FL OZ (177mL)